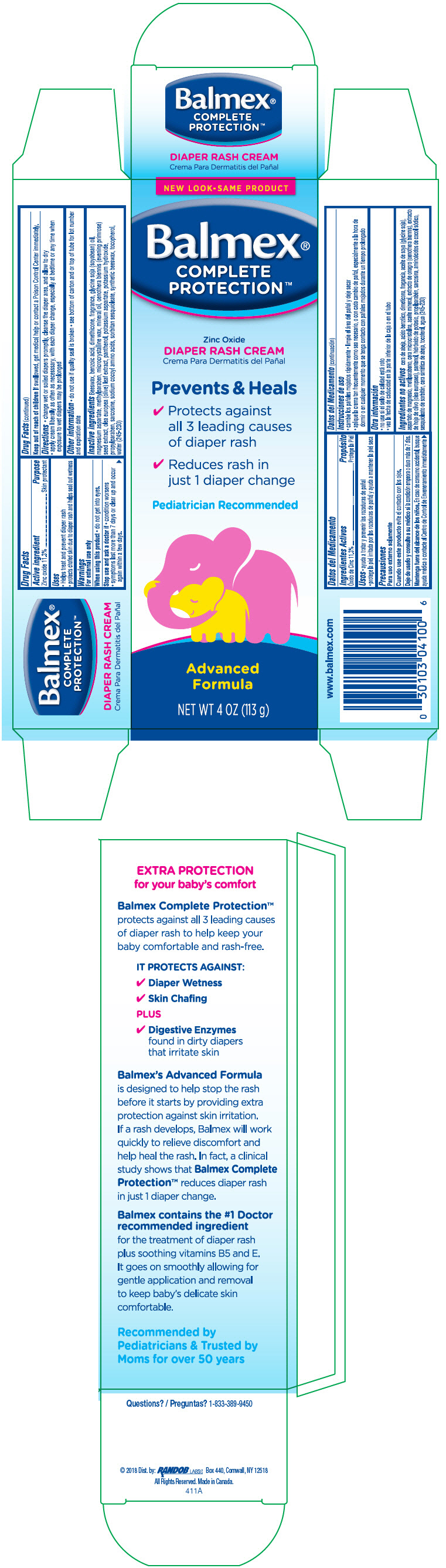 DRUG LABEL: Balmex Diaper Rash
NDC: 52412-400 | Form: CREAM
Manufacturer: Randob Labs,Ltd.
Category: otc | Type: HUMAN OTC DRUG LABEL
Date: 20181113

ACTIVE INGREDIENTS: Zinc Oxide 0.113 g/1 g
INACTIVE INGREDIENTS: Yellow Wax; Benzoic Acid; Dimethicone 100; Soybean Oil; Magnesium Aspartate Anhydrous; Methylparaben; Microcrystalline Wax; Mineral Oil; Oenothera Biennis; Olea Europaea Leaf; Dexpanthenol; Potassium Aspartate; Potassium Hydroxide; Propylene Glycol; Propylparaben; Sarcosine; Sorbitan Sesquioleate; Tocopherol; Water; Sodium Cocoyl Glycinate; White Wax

Balmex® Diaper Rash

Drug Facts

ACTIVE INGREDIENT

Active ingredients | Purpose
Zinc Oxide 11.3% | Skin protectant

Uses

- Helps treat and prevent diaper rash
- protects chafed skin due to diaper rash and helps seal out wetness

Warnings

For external use only

When using this product

- do not get into eyes.

Stop use and ask a doctor if

- condition worsens
- symptoms last more than 7 days or clear up and occur again within a few days.

Keep out of reach of children. If swallowed, get medical help or contact a Poison Control Center immediately.

Directions

- change wet or soiled diapers promptly, cleanse the diaper area, and allow to dry
- apply cream liberally as often as necessary, with each diaper change, especially at bedtime or any time when exposure to wet diapers may be prolonged

Other information

- do not use if quality seal is broken
- see bottom of carton and or top of tube for lot number and expiration date

INACTIVE INGREDIENT

Inactive ingredients Beeswax, benzoic acid, dimethicone, fragrance, glycine soja (soybean) oil, magnesium aspartate, methylparaben, microcrystalline wax, mineral oil, oenothera biennis (evening primrose) seed extract, olea europea (olive) leaf extract, panthenol, potassium aspartate, potassium hydroxide, propylparaben, sarcosine, sodium cocoyl amino acids, sorbitan sesquioleate, synthetic beeswax, tocopherol, water (245-230)

Questions?

1-833-389-9450
Dist. by: RANDOB LABS LTD. Box 440, Cornwall, NY 12518

PRINCIPAL DISPLAY PANEL - 113 g Tube Carton

NEW LOOK-SAME PRODUCT

Balmex®
COMPLETE
PROTECTION™

Zinc Oxide

DIAPER RASH CREAM

Prevents & Heals

✔ Protects against
  all 3 leading causes
  of diaper rash
✔ Reduces rash in
  just 1 diaper change

Pediatrician Recommended

Advanced
Formula

NET WT 4 OZ (113 g)